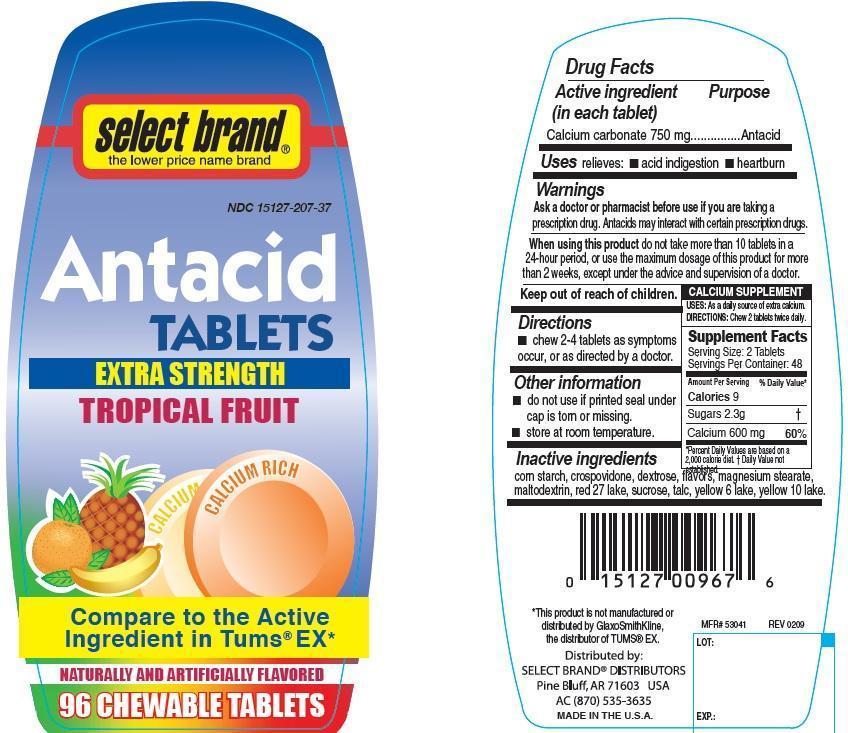 DRUG LABEL: Antacid
NDC: 15127-207 | Form: TABLET, CHEWABLE
Manufacturer: Select Brand
Category: otc | Type: HUMAN OTC DRUG LABEL
Date: 20141001

ACTIVE INGREDIENTS: CALCIUM CARBONATE 750 mg/1 1
INACTIVE INGREDIENTS: STARCH, CORN; CROSPOVIDONE; D&C RED NO. 27; D&C YELLOW NO. 10; DEXTROSE; FD&C YELLOW NO. 6; MAGNESIUM STEARATE; MALTODEXTRIN; SUCROSE; TALC

Select Brand Extra Strength Tropical Fruit Antacid tablets

Active ingredient (in each tablet)

Calcium carbonate 750 mg

Purpose

Antacid

Uses

relieves

- acid indigestion
- heartburn

Warnings

Ask a doctor or pharmacist before use if you are

taking a prescription drug. Antacids may interact with certain prescription drugs.

When using this product

do not take more than 10 tablets in a 24 hour period, or use the maximum dosage of this product for more than 2 weeks, except under the advice and supervision of a doctor.

Keep out of reach of children.

Directions

- chew 2-4 tablets as symptoms occur, or as directed by a doctor.

Other information

- do not use if printed seal under cap is torn or missing.
- store at room temperature.

Inactive ingredients

corn starch, crospovidone, red 27 lake, yellow 10 lake, dextrose, yellow 6 lake, flavors, magnesium stearate, maltodextrin, sucrose, talc

Principal Display Panel

Select Brand

Antacid Tablets

Extra Strength

TROPICAL FRUIT

Compare to the Active ingredient in TUMS® EX

Naturally and Artificially Flavored

96 CHEWABLE TABLETS